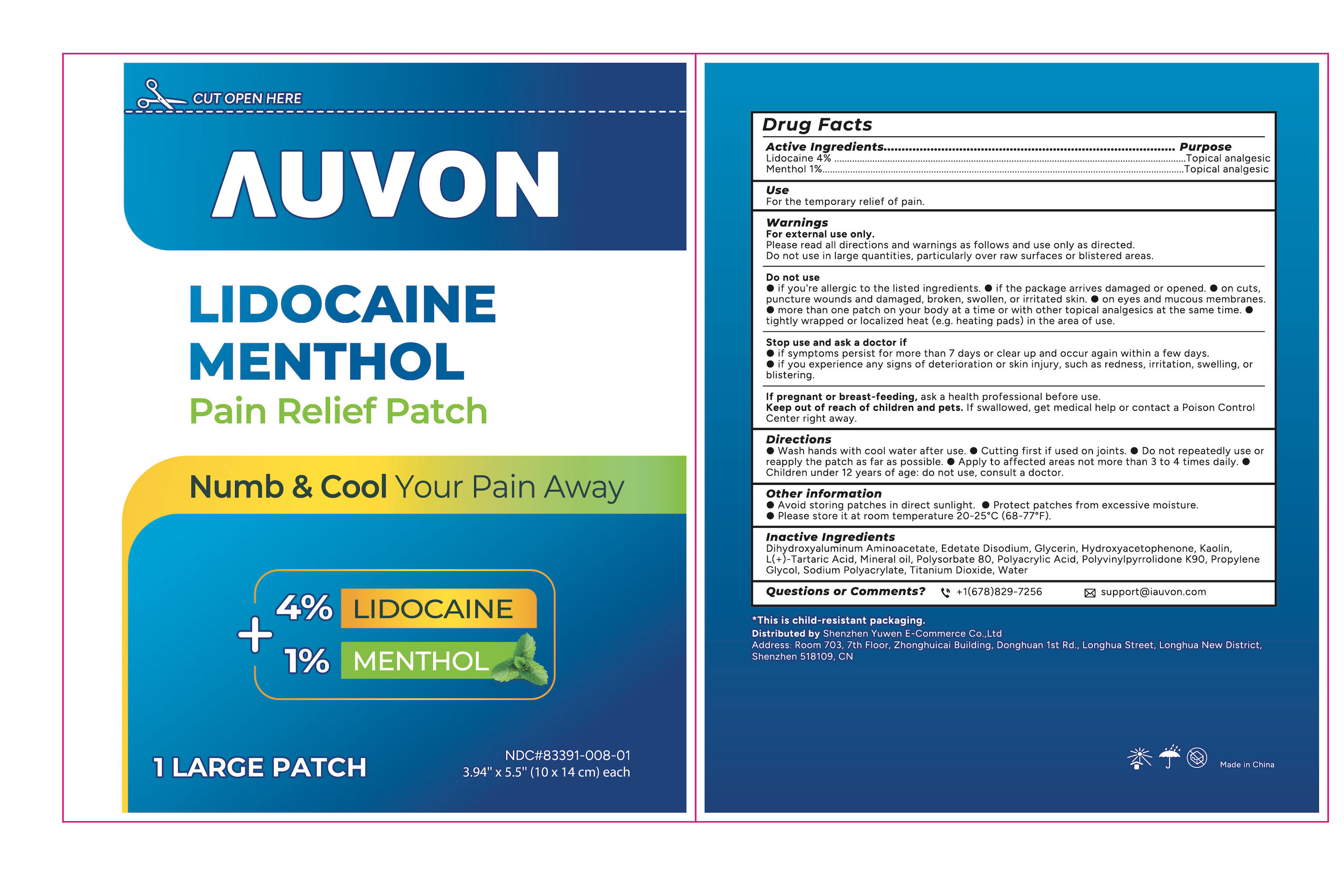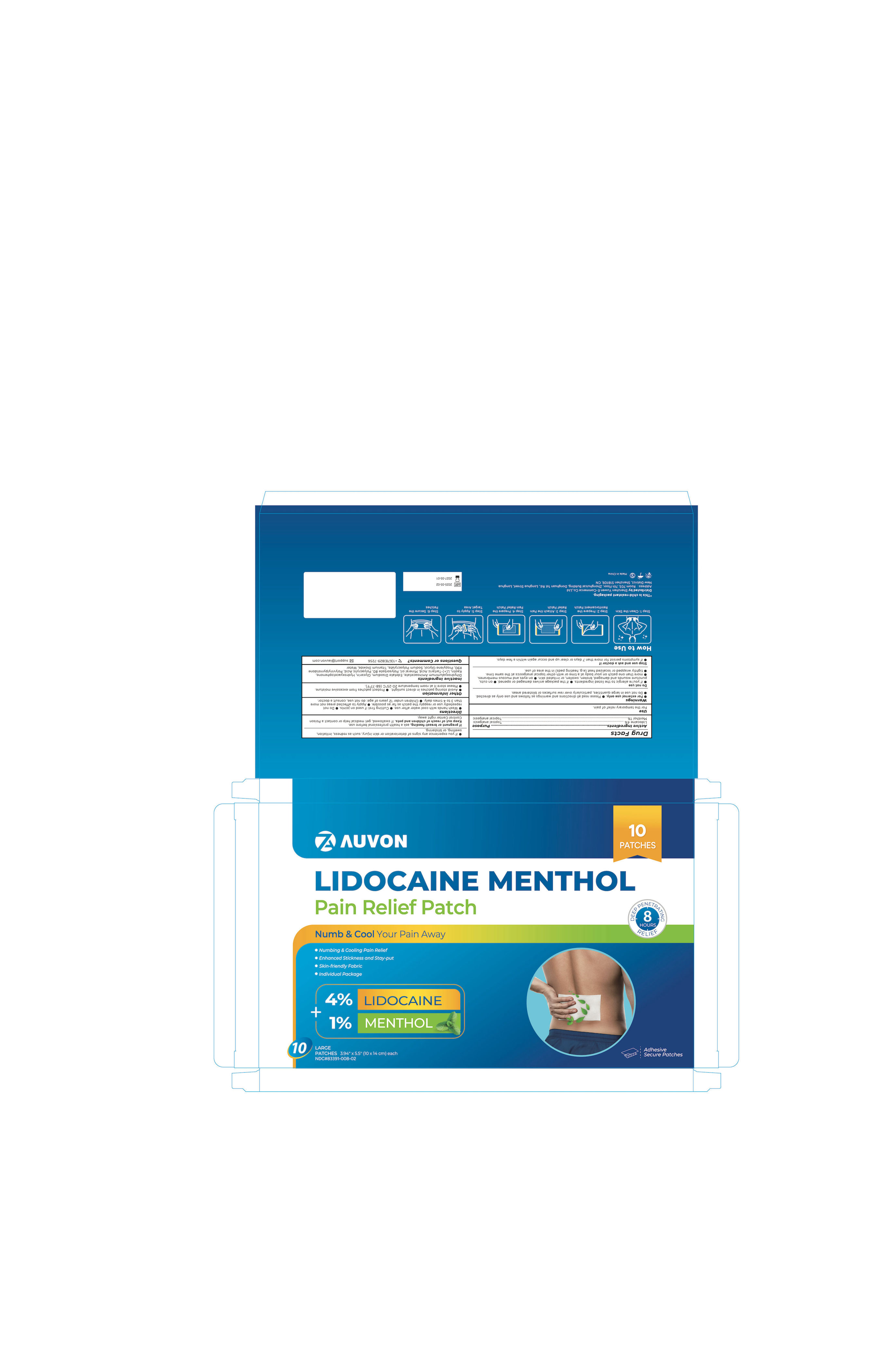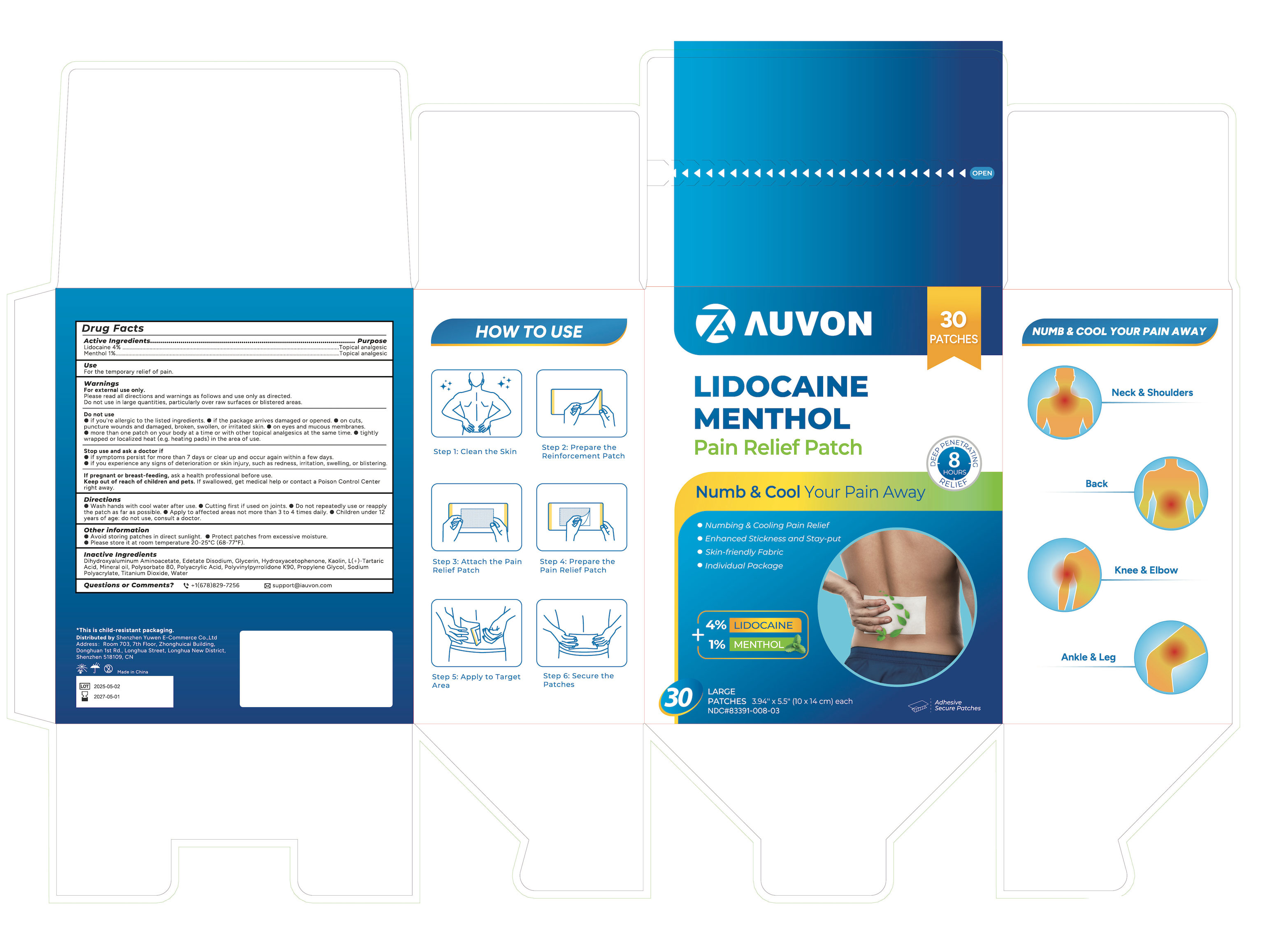 DRUG LABEL: AUVON Lidocaine Menthol Pain Relief Patch
NDC: 83391-008 | Form: PATCH
Manufacturer: SHENZHEN YUWEN E-COMMERCE CO., LTD.
Category: otc | Type: HUMAN OTC DRUG LABEL
Date: 20250320

ACTIVE INGREDIENTS: LEVOMENTHOL 100 mg/1 1; LIDOCAINE 400 mg/1 1
INACTIVE INGREDIENTS: TITANIUM DIOXIDE; PROPYLENE GLYCOL; MINERAL OIL; POLYACRYLIC ACID (250000 MW); WATER; KAOLIN; HYDROXYACETOPHENONE; POLYSORBATE 80; GLYCERIN; DIHYDROXYALUMINUM AMINOACETATE; SODIUM POLYACRYLATE (2500000 MW); EDETATE DISODIUM; TARTARIC ACID; POVIDONE K90

83391-008

AUVON LIDOCAINE MENTHOL Pain Relief Patch

ACTIVE INGREDIENT

Lidocaine 4%

Menthol 1%

PURPOSE

Topical anesthetic

INDICATIONS AND USAGE

for the temporary pain relief

WARNINGS

For external use only

DO NOT USE

If you are allergic to the listed ingredients

If you are pregnent or breast feeding

If you are under 12 years of age

On wounds, cuts, damaged/broken/irritated skin

On eyes or mucous membranes

With heating pads/devices or wrap with a bandage

With other topical analgesics

If the package arrives damaged or opened.

WHEN USING

■ Read and follow all directions and warnings on this label

■ avoid contact with the eyes and mucous membranes

■ rare cases of serious burns have been reported with products of this type

■ a transient burning sensation may occur upon application but generally disappears in several days

■ dispose of used patch in manner that always keeps product away from children and pets. Used patches still contain the drug product that can produce serious adverse effects if a child or pet chews or ingests this patch.

STOP USE

You are experiencing pain, swelling or blistering

Redness is persent or irritation develops

Symptoms persist for more than 7 days or clear up and occur again within a few days

KEEP OUT OF REACH OF CHILDREN

Children under 12years of age: do not use, consult a doctor.

DOSAGE AND ADMINISTRATION

■ Clean and dry the patch application area (no wound or hair), pull to separate the film, peel off one side of the film, apply the exposed patch to the skin, peel off the ■ Do not repeatedly use or repeatedly reapply the patch as far as possible

■ Cut first if if used on joints

■ Use in te affected area no more than 4 times daily

■ Wash hands with cool water after use

STORAGE AND HANDLING

Avoid storing patches in direct sunlight

Protect patches from excessive moisture.

Store it at room temperature 20-25°c

INACTIVE INGREDIENT

Dihydroxyaluminum Aminoacetate

Edetate Disodium

Glycerin

Hydroxyacetophenone

Kaolin

L(+)-Tartaric Acid

Mineral oil

Polysorbate 80

Polyacrylic Acid

Polyvinylpyrrolidone K90

Propylene Glycol

Sodium Polyacrylate

Titanium Dioxide

Water